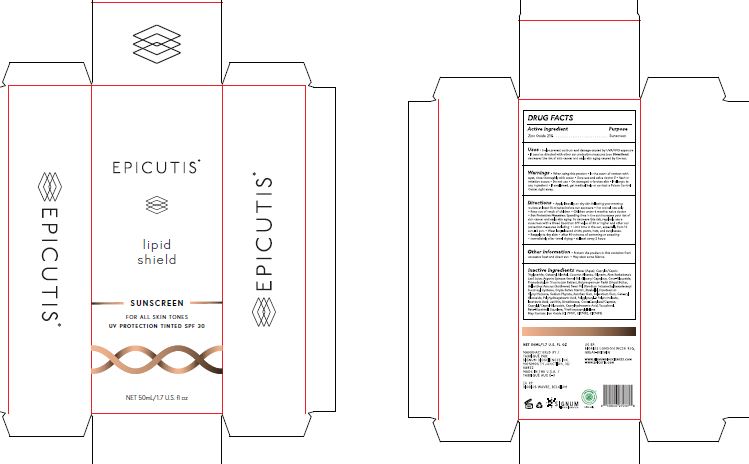 DRUG LABEL: Lipid Shield SPF 30
NDC: 62742-4273 | Form: CREAM
Manufacturer: Allure Labs
Category: otc | Type: HUMAN OTC DRUG LABEL
Date: 20250807

ACTIVE INGREDIENTS: ZINC OXIDE 21 g/100 g
INACTIVE INGREDIENTS: GLYCERYL CAPRYLATE; TOCOPHEROL; PHAEODACTYLUM TRICORNUTUM; SHEA BUTTER; DISODIUM TETRAMETHYLHEXADECENYL SUCCINOYL CYSTEINE; COCONUT ALKANES; DIPOTASSIUM GLYCYRRHIZATE; CI 77499; ALOE BARBADENSIS LEAF JUICE; COCO-GLUCOSIDE; HELIANTHUS ANNUUS (SUNFLOWER) SEED OIL; BISABOLOL; XANTHAN GUM; SCLEROTIUM GUM; ISOSTEARIC ACID; LECITHIN, SOYBEAN; CAPRYLYL/CAPRYL GLUCOSIDE; CAPRYLIC/CAPRIC TRIGLYCERIDE; GLYCERIN; WATER; CETEARYL ALCOHOL; CAPRYLHYDROXAMIC ACID; .BETA.-SITOSTEROL; CI 77492; POLYGLYCERYL-3 PENTARICINOLEATE; ORYZA SATIVA (RICE) STARCH; POLYHYDROXYSTEARIC ACID (2300 MW); CETEARYL GLUCOSIDE; ARGANIA SPINOSA KERNEL OIL; SODIUM PHYTATE; DIMETHICONE; COCO-CAPRYLATE/CAPRATE; TRIETHOXYCAPRYLYLSILANE; CI 77491; SQUALENE

Drug Facts

Active Ingredient: Zinc Oxide 21%

Purpose: Sunscreen

INDICATIONS AND USAGE

Uses • Helps prevent sunburn and damage caused by UVA/UVB exposure • If used as directed with other sun protection measures (see Directions) decreases the risk of skin cancer and early skin aging caused by the sun.

WARNINGS

.

Do not use on damaged or broken skin

When using this product In the event of contact with eyes, rinse thoroughly with water

Stop use and ask a doctor if Rash or irritation occurs

KEEP OUT OF REACH OF CHILDREN

If swallowed, get medical help or contact a Poison Control Center right away

DOSAGE AND ADMINISTRATION

Directions • Apply liberally on dry skin following your morning routine at least 15 minutes before sun exposure • For topical use only • Keep out of reach of children • Children under 6 months: ask a doctor • Sun Protection Measures: Spending time in the sun increases your risk of skin cancer and early skin aging. To decrease this risk, regularly use a sunscreen with a Broad Spectrum SPF value of 30 or higher and other sun protection measures including: • Limit time in the sun, especially from 10 a.m. - 2 p.m. • Wear long-sleeved shirts, pants, hats, and sunglasses. • Reapply to dry skin: • after 80 minutes of swimming or sweating • immediately after towel drying • at least every 2 hours

Other Information • Protect the product in this container from excessive heat and direct sun. • May stain some fabrics.

INACTIVE INGREDIENT

Inactive Ingredients: Water (Aqua), Caprylic/Capric Triglyceride, Cetearyl Alcohol, Coconut Alkanes, Glycerin, Aloe Barbadensis Leaf Juice, Argania Spinosa Kernel Oil, Glyceryl Caprylate, Coco-Glucoside, Phaeodactylum Tricornutum Extract, Butyrospermum Parkii (Shea) Butter, Helianthus Annuus (Sunflower) Seed Oil, Disodium Tetramethylhexadecenyl Succinoyl Cysteine, Oryza Sativa Starch, Bisabolol, Dipotassium Glycyrrhizinate, Sodium Phytate, Xanthan Gum, Sclerotium Gum, Cetearyl Glucoside, Polyhydroxystearic Acid, Polyglyceryl-3 Polyricinoleate, Isostearic Acid, Lecithin, Dimethicone, Coco-Caprylate/Caprate, Caprylyl/Capryl Glucoside, Caprylhydroxamic Acid, Tocopherol, Beta-Sitosterol, Squalene, Triethoxycaprylylsilane
May Contain: Iron Oxide (CI 77491, CI77492, CI77499)